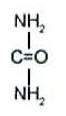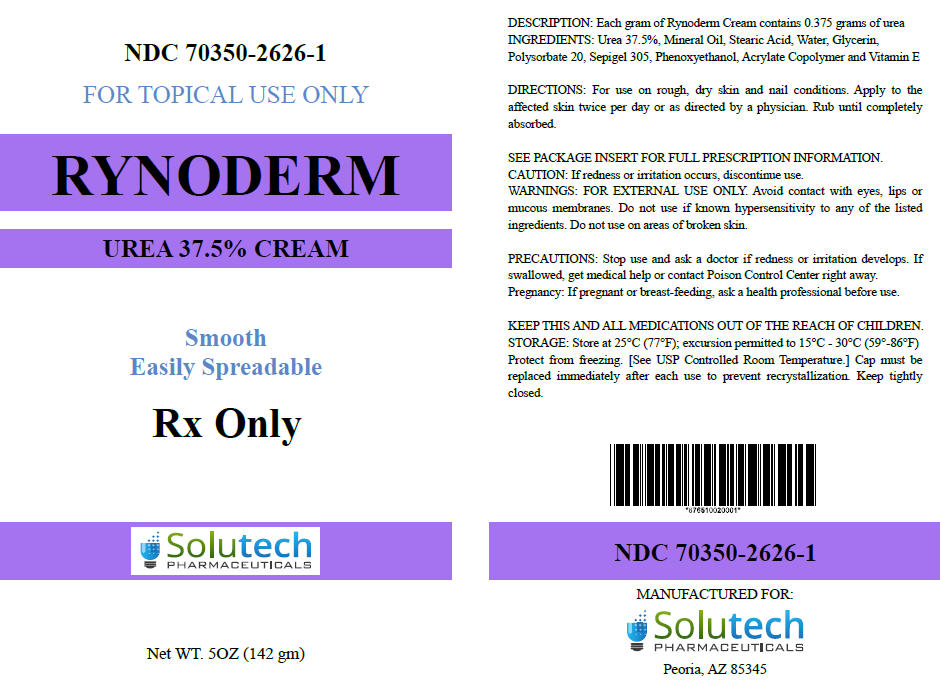 DRUG LABEL: RYNODERM
NDC: 70350-2626 | Form: CREAM
Manufacturer: SOLUTECH PHARMACEUTICALS LLC
Category: prescription | Type: HUMAN PRESCRIPTION DRUG LABEL
Date: 20171027

ACTIVE INGREDIENTS: UREA 375 mg/1 g
INACTIVE INGREDIENTS: MINERAL OIL; STEARIC ACID; WATER; GLYCERIN; POLYSORBATE 20; SODIUM ACRYLOYLDIMETHYLTAURATE-ACRYLAMIDE COPOLYMER (1:1; 90000-150000 MPA.S); PHENOXYETHANOL; .ALPHA.-TOCOPHEROL

RYNODERM CREAM
(Urea 37.5% in a cream base)

Rx only

For external use only.
Not for ophthalmic use.

RYNODERM Description

Rynoderm cream is a potent keratolytic emollient which is a gentle, yet potent, tissue softener for skin and/or nails.

Each gram of Rynoderm Cream contains:

ACTIVE: 37.5% Urea in a cream base of:

INACTIVES: Mineral Oil, Stearic Acid, Water, Glycerin, Polysorbate 20, Sepigel 305, Phenoxyethanol, Acrylate Copolymer and Vitamin E

CHEMISTRY

Urea is a diamide of carbonic acid with the following chemical structure:

RYNODERM - Clinical Pharmacology

Urea gently dissolves the intercellular matrix which results in loosening the horny layer of skin and shedding scaly skin at regular intervals, thereby softening hyperkeratotic areas. Urea also hydrates and gently dissolves the intercellular matrix of the nail plate, which can result in the softening and eventual debridement of the nail plate.

PHARMACOKINETICS

The mechanism of action of topically applied urea is not yet known.

INDICATIONS AND USES

For debridement and promotion of normal healing of hyperkeratotic surface lesions, particularly where healing is retarded by local infection, necrotic tissue, fibrinous or prurient debris or eschar. Urea is useful for the treatment of hyperkeratotic conditions such as dry, rough skin, dermatitis, psoriasis, xerosis, ichthyosis, eczema, keratosis, keratoderma, corns and calluses, as well as damaged, ingrown and devitalized nails.

Contraindications

Rynoderm Cream is contraindicated in patients with known hypersensitivity to any of the listed ingredients.

Warnings

For external use only. Avoid contact with eyes, lips or mucous membranes. Do not use on areas of broken skin.

Precautions

After applying this medication, wash hands and unaffected areas thoroughly. Stop use and ask a doctor if redness or irritation develops. If swallowed, get medical help or contact Poison Control Center right away. KEEP THIS AND ALL MEDICATION OUT OF THE REACH OF CHILDREN.

PREGNANCY

Pregnancy Category B

Animal reproduction studies have revealed no evidence of harm to the fetus, however, there are no adequate and well-controlled studies in pregnant women. Because animal reproduction studies are not always predictive of human response, Rynoderm Cream should be given to a pregnant woman only if clearly needed.

NURSING MOTHERS

It is not known whether or not this drug is secreted in human milk. Because many drugs are secreted in human milk, caution should be exercised when Rynoderm Cream is administered to a nursing woman.

Adverse Reactions

Transient stinging, burning, itching or irritation may occur and normally disappear on discontinuing the medication.

RYNODERM - Dosage and Administration

Apply Rynoderm Cream to affected skin twice per day or as directed by a physician. Rub in until completely absorbed. Apply to diseased or damaged nail tissue twice per day or as directed by a physician.

How is RYNODERM Supplied

RYNODERM Cream (37.5% urea) is supplied in:

142g (5 oz) tube | 70350-2626-1

STORAGE AND HANDLING

Store at 25°C (77°F); excursion permitted to 15°C - 30°C (59° - 86°F) Protect from freezing. [See USP Controlled Room Temperature.]

Manufactured for:
Solutech Pharmaceuticals LLC
Peoria, AZ 85345

Rx only

PRINCIPAL DISPLAY PANEL - 142 gm Tube Label

NDC 70350-2626-1

FOR TOPICAL USE ONLY

RYNODERM
UREA 37.5% CREAM

Smooth
Easily Spreadable

Rx only

Solutech
PHARMACEUTICALS

Net WT. 5OZ (142 gm)